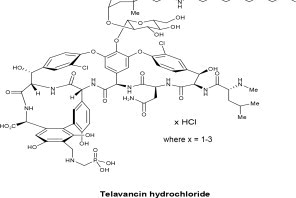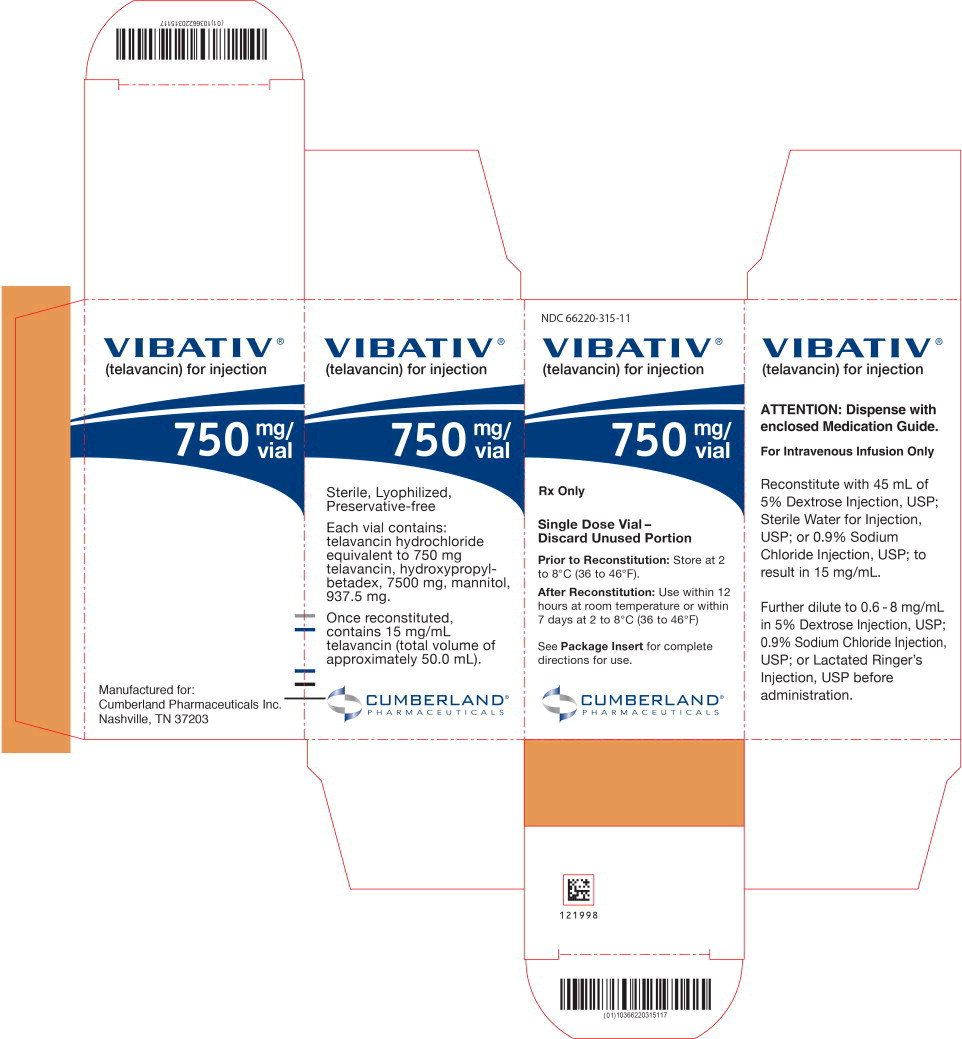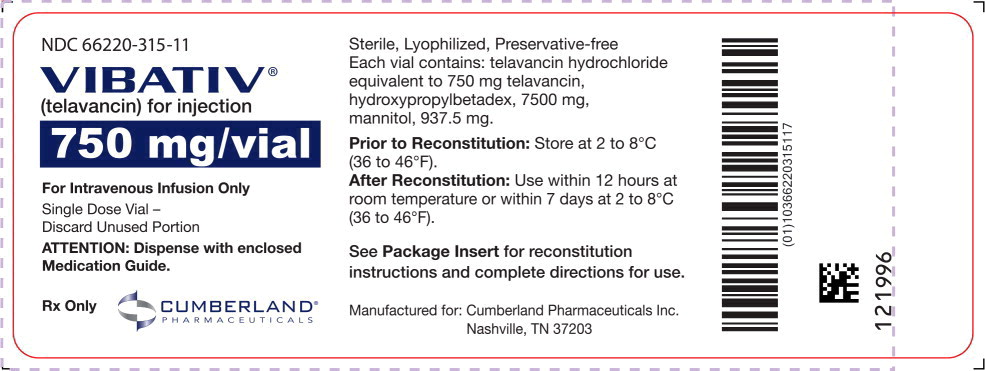 DRUG LABEL: VIBATIV
NDC: 66220-315 | Form: INJECTION, POWDER, LYOPHILIZED, FOR SOLUTION
Manufacturer: Cumberland Pharmaceuticals Inc.
Category: prescription | Type: HUMAN PRESCRIPTION DRUG LABEL
Date: 20251219

ACTIVE INGREDIENTS: telavancin hydrochloride 15 mg/1 mL
INACTIVE INGREDIENTS: HYDROXYPROPYL BETADEX; MANNITOL; SODIUM HYDROXIDE; HYDROCHLORIC ACID

HIGHLIGHTS OF PRESCRIBING INFORMATION

These highlights do not include all the information needed to use VIBATIV® (telavancin) safely and effectively. See full prescribing information for VIBATIV.
VIBATIV® (telavancin) for injection, for intravenous use
Initial U.S. Approval: 2009

WARNING: INCREASED MORTALITY IN HABP/VABP PATIENTS WITH PRE-EXISTING MODERATE OR SEVERE RENAL IMPAIRMENT, NEPHROTOXICITY, POTENTIAL ADVERSE DEVELOPMENTAL OUTCOMES

WARNING: INCREASED MORTALITY IN HABP/VABP PATIENTS WITH PRE-EXISTING MODERATE OR SEVERE RENAL IMPAIRMENT, NEPHROTOXICITY, and EMBRYO-FETAL TOXICITY

See full prescribing information for the complete boxed warning

- Patients with pre-existing moderate/severe renal impairment (CrCl≤50 mL/min) who were treated with VIBATIV for hospital-acquired bacterial pneumonia/ventilator-associated bacterial pneumonia had increased mortality observed versus vancomycin. Use of VIBATIV in patients with pre-existing moderate/severe renal impairment (CrCl ≤50 mL/min) should be considered only when the anticipated benefit to the patient outweighs the potential risk. (5.1, 8.4)
- Nephrotoxicity: New onset or worsening renal impairment has occurred. Monitor renal function in all patients. (5.3)
- Embryo-Fetal Toxicity: VIBATIV may cause fetal harm. In animal reproduction studies, adverse developmental outcomes were observed in 3 animal species at clinically relevant doses. Verify pregnancy status prior to initiating treatment and advise females of reproductive potential to use effective contraception (5.4, 8.1, 8.3).

1 INDICATIONS AND USAGE

VIBATIV is a lipoglycopeptide antibacterial drug indicated for the treatment of the following infections in adult patients caused by designated susceptible bacteria:

- Complicated skin and skin structure infections (cSSSI) (1.1)
- Hospital-acquired and ventilator-associated bacterial pneumonia (HABP/VABP) caused by susceptible isolates of Staphylococcus aureus. VIBATIV should be reserved for use when alternative treatments are not suitable. (1.2)

To reduce the development of drug-resistant bacteria and maintain the effectiveness of VIBATIV and other antibacterial drugs VIBATIV should only be used to treat or prevent infections that are proven or strongly suspected to be caused by bacteria.

2 DOSAGE AND ADMINISTRATION

- Complicated skin and skin structure infections (cSSSI):
  - 10 mg/kg by IV infusion over 60 minutes every 24 hours for 7 to 14 days (2.1)
  - Dosage adjustment in patients with renal impairment. (2.3)
- Hospital-acquired and ventilator-associated bacterial pneumonia (HABP/VABP):
  - 10 mg/kg by IV infusion over 60 minutes every 24 hours for 7 to 21 days (2.2)
  - Dosage adjustment in patients with renal impairment. (2.3)

Creatinine Clearancea (CrCl) (mL/min) | VIBATIV Dosage Regimen
>50 | 10 mg/kg every 24 hours
30-50 | 7.5 mg/kg every 24 hours
10-<30 | 10 mg/kg every 48 hours
aCalculate using the Cockcroft-Gault formula and ideal body weight (IBW). Use actual body weight if < IBW. (12.3)

Insufficient data are available to make a dosing recommendation for patients with CrCl <10 mL/min, including patients on hemodialysis.

3 DOSAGE FORMS AND STRENGTHS

Single-dose vials containing 750 mg telavancin. (3)

4 CONTRAINDICATIONS

- Intravenous Unfractionated Heparin Sodium (4.1, 5.5, 7.1)
- Known hypersensitivity to VIBATIV (4.2, 5.6, 6.2)

5 WARNINGS AND PRECAUTIONS

- Decreased efficacy among patients treated for skin and skin structure infections with moderate/severe pre-existing renal impairment: Consider these data when selecting antibacterial therapy for patients with baseline CrCl ≤50 mL/min. (5.2)
- Coagulation test interference: Telavancin interferes with some laboratory coagulation tests, including prothrombin time, international normalized ratio, and activated partial thromboplastin time. (5.5, 7.1)
- Hypersensitivity reactions: Serious and potentially fatal hypersensitivity reactions, including anaphylactic reactions, may occur after first or subsequent doses. VIBATIV should be used with caution in patients with known hypersensitivity to vancomycin. (5.6, 6.2)
- Infusion-related reactions: Administer VIBATIV over at least 60 minutes to minimize infusion-related reactions. (5.7)
- Clostridium difficile-Associated Diarrhea: May range from mild diarrhea to fatal colitis. Evaluate if diarrhea occurs. (5.8)
- QTc prolongation: Avoid use in patients at risk. Use with caution in patients taking drugs known to prolong the QT interval. (5.10)

6 ADVERSE REACTIONS

Most common adverse reaction (≥10% of patients treated with VIBATIV) in the HABP/VABP trials is diarrhea; in the cSSSI trials, the most common adverse reactions (≥10% of patients treated with VIBATIV) include: taste disturbance, nausea, vomiting, and foamy urine. (6.1)

To report SUSPECTED ADVERSE REACTIONS, contact Cumberland Pharmaceuticals Inc. at 1-877-683-6110 or FDA at 1-800-FDA-1088 or www.fda.gov/medwatch.

8 USE IN SPECIFIC POPULATIONS

Pediatric patients: Safety and efficacy have not been established. (8.4)

FULL PRESCRIBING INFORMATION

WARNING: INCREASED MORTALITY IN HABP/VABP PATIENTS WITH PRE-EXISTING MODERATE OR SEVERE RENAL IMPAIRMENT, NEPHROTOXICITY, POTENTIAL ADVERSE DEVELOPMENTAL OUTCOMES

- Patients with pre-existing moderate/severe renal impairment (CrCl ≤ 50 mL/min) who were treated with VIBATIV for hospital-acquired bacterial pneumonia/ventilator-associated bacterial pneumonia (HABP/VABP) had increased mortality observed versus vancomycin. Use of VIBATIV in patients with pre-existing moderate/severe renal impairment (CrCl ≤ 50 mL/min) should be considered only when the anticipated benefit to the patient outweighs the potential risk [see Warnings and Precautions (5.1, 8.4)].
- Nephrotoxicity: New onset or worsening renal impairment has occurred. Monitor renal function in all patients [see Warnings and Precautions (5.3)].
- Embryofetal Toxicity: VIBATIV may cause fetal harm. In animal reproduction studies, adverse developmental outcomes were observed in 3 animal species at clinically relevant doses. Verify pregnancy status in females of reproductive potential prior to initiating VIBATIV. Advise pregnant women of the potential risk to a fetus. Advise females of reproductive potential to use effective contraception during treatment with VIBATIV and for 2 days after the final dose [see Warnings and Precautions (5.1), and Use in Specific Populations (8.1, 8.3)].

1 INDICATIONS AND USAGE

1.1 Complicated Skin and Skin Structure Infections

VIBATIV is indicated for the treatment of adult patients with complicated skin and skin structure infections (cSSSI) caused by susceptible isolates of the following Gram-positive microorganisms: Staphylococcus aureus (including methicillin-susceptible and -resistant isolates), Streptococcus pyogenes, Streptococcus agalactiae, Streptococcus anginosus group (includes S. anginosus, S. intermedius, and S. constellatus), or Enterococcus faecalis (vancomycinsusceptible isolates only).

1.2 HABP/VABP

VIBATIV is indicated for the treatment of adult patients with hospital-acquired and ventilator-associated bacterial pneumonia (HABP/VABP), caused by susceptible isolates of Staphylococcus aureus (both methicillin-susceptible and -resistant isolates). VIBATIV should be reserved for use when alternative treatments are not suitable.

1.3 Usage

Combination therapy may be clinically indicated if the documented or presumed pathogens include Gram-negative organisms.

Appropriate specimens for bacteriological examination should be obtained in order to isolate and identify the causative pathogens and to determine their susceptibility to telavancin. VIBATIV may be initiated as empiric therapy before results of these tests are known.

To reduce the development of drug-resistant bacteria and maintain the effectiveness of VIBATIV and other antibacterial drugs, VIBATIV should be used only to treat infections that are proven or strongly suspected to be caused by susceptible bacteria. When culture and susceptibility information are available, they should be considered in selecting or modifying antibacterial therapy. In the absence of such data, local epidemiology and susceptibility patterns may contribute to the empiric selection of therapy.

2 DOSAGE AND ADMINISTRATION

2.1 Complicated Skin and Skin Structure Infections

The recommended dosing for VIBATIV is 10 mg/kg administered over a 60-minute period in patients ≥18 years of age by intravenous infusion once every 24 hours for 7 to 14 days. The duration of therapy should be guided by the severity and site of the infection and the patient's clinical progress.

2.2 Hospital-Acquired Bacterial Pneumonia/Ventilator-Associated Bacterial Pneumonia (HABP/VABP)

The recommended dosing for VIBATIV is 10 mg/kg administered over a 60-minute period in patients ≥18 years of age by intravenous infusion once every 24 hours for 7 to 21 days. The duration of therapy should be guided by the severity of the infection and the patient's clinical progress.

2.3 Patients with Renal Impairment

Because telavancin is eliminated primarily by the kidney, a dosage adjustment is required for patients whose creatinine clearance is ≤50 mL/min, as listed in Table 1 [see Clinical Pharmacology (12.3)].

Table 1: Dosage Adjustment in Adult Patients with Renal Impairment
Creatinine Clearancea (CrCl) (mL/min) | VIBATIV Dosage Regimen
>50 | 10 mg/kg every 24 hours
30-50 | 7.5 mg/kg every 24 hours
10-<30 | 10 mg/kg every 48 hours
aCalculate using the Cockcroft-Gault formula and ideal body weight (IBW). Use actual body weight if it is less than IBW. (12.3)

There is insufficient information to make specific dosage adjustment recommendations for patients with end-stage renal disease (CrCl <10 mL/min), including patients undergoing hemodialysis.

2.4 Preparation and Administration

750 mg vial: Reconstitute the contents of a VIBATIV 750 mg vial with 45 mL of 5% Dextrose Injection, USP; Sterile Water for Injection, USP; or 0.9% Sodium Chloride Injection, USP. The resultant solution has a concentration of 15 mg/mL (total volume of approximately 50.0 mL).

To minimize foaming during product reconstitution, allow the vacuum of the vial to pull the diluent from the syringe into the vial. Do not forcefully inject the diluent into the vial. Do not forcefully shake the vial and do not shake final infusion solution.

The following formula can be used to calculate the volume of reconstituted VIBATIV solution required to prepare a dose:

Telavancin dose (mg) = 10 mg/kg or 7.5 mg/kg x patient weight (in kg) (see Table 1)

Volume of reconstituted solution (mL) = | Telavancin dose (mg)
 | 15 mg/mL

For doses of 150 to 800 mg, the appropriate volume of reconstituted solution must be further diluted in 100 to 250 mL prior to infusion. Doses less than 150 mg or greater than 800 mg should be further diluted in a volume resulting in a final concentration of 0.6 to 8 mg/mL. Appropriate infusion solutions include: 5% Dextrose Injection, USP; 0.9% Sodium Chloride Injection, USP; or Lactated Ringer's Injection, USP. The dosing solution should be administered by intravenous infusion over a period of 60 minutes.

Reconstitution time is generally under 2 minutes, but can sometimes take up to 20 minutes. Mix thoroughly to reconstitute and check to see if the contents have dissolved completely. Parenteral drug products should be inspected visually for particulate matter prior to administration. Discard the vial if the vacuum did not pull the diluent into the vial.

Since no preservative or bacteriostatic agent is present in this product, aseptic technique must be used in preparing the final intravenous solution. Studies have shown that the reconstituted solution in the vial should be used within 12 hours when stored at room temperature or within 7 days under refrigeration at 2 to 8°C (36 to 46°F). The diluted (dosing) solution in the infusion bag should be used within 12 hours when stored at room temperature or used within 7 days when stored under refrigeration at 2 to 8°C (36 to 46°F). However, the total time in the vial plus the time in the infusion bag should not exceed 12 hours at room temperature and 7 days under refrigeration at 2 to 8°C (36 to 46°F). The diluted (dosing) solution in the infusion bag can also be stored at -30 to -10°C (-22 to 14°F) for up to 32 days.

VIBATIV is administered intravenously. Because only limited data are available on the compatibility of VIBATIV with other IV substances, additives or other medications should not be added to VIBATIV single-dose vials or infused simultaneously through the same IV line. If the same intravenous line is used for sequential infusion of additional medications, the line should be flushed before and after infusion of VIBATIV with 5% Dextrose Injection, USP; 0.9% Sodium Chloride Injection, USP; or Lactated Ringer's Injection, USP.

3 DOSAGE FORMS AND STRENGTHS

VIBATIV is supplied in single-dose vials containing 750 mg telavancin as a sterile, lyophilized powder.

4 CONTRAINDICATIONS

4.1 Intravenous Unfractionated Heparin Sodium

Use of intravenous unfractionated heparin sodium is contraindicated with VIBATIV administration because the activated partial thromboplastin time (aPTT) test results are expected to be artificially prolonged for 0 to 18 hours after VIBATIV administration [see Warnings and Precautions (5.5) and Drug Interactions (7.1)].

4.2 Known Hypersensitivity to VIBATIV

VIBATIV is contraindicated in patients with known hypersensitivity to telavancin.

5 WARNINGS AND PRECAUTIONS

5.1 Increased Mortality in Patients with HABP/VABP and Pre-existing Moderate to Severe Renal Impairment (CrCl ≤50 mL/min)

In the analysis of patients (classified by the treatment received) in the two combined HABP/VABP trials with preexisting moderate/severe renal impairment (CrCl ≤50 mL/min), all-cause mortality within 28 days of starting treatment was 95/241 (39%) in the VIBATIV group, compared with 72/243 (30%) in the vancomycin group. Allcause mortality at 28 days in patients without pre-existing moderate/severe renal impairment (CrCl >50 mL/min) was 86/510 (17%) in the VIBATIV group and 92/510 (18%) in the vancomycin group. Therefore, VIBATIV use in patients with baseline CrCl ≤50 mL/min should be considered only when the anticipated benefit to the patient outweighs the potential risk [see Adverse Reactions (6.1), Use in Specific Populations (8.4) and Clinical Studies (14.2)].

5.2 Decreased Clinical Response in Patients with cSSSI and Pre-existing Moderate/Severe Renal Impairment (CrCl ≤50 mL/min)

In a subgroup analysis of the combined cSSSI trials, clinical cure rates in the VIBATIV-treated patients were lower in patients with baseline CrCl ≤50 mL/min compared with those with CrCl >50 mL/min (Table 2). A decrease of this magnitude was not observed in vancomycin-treated patients. Consider these data when selecting antibacterial therapy for use in patients with cSSSI and with baseline moderate/severe renal impairment.

Table 2: Clinical Cure by Pre-existing Renal Impairment – Clinically Evaluable Population
 | VIBATIV % (n/N) | Vancomycin % (n/N)
cSSSI Trials
CrCl >50 mL/min | 87.0% (520/598) | 85.9% (524/610)
CrCl ≤50 mL/min | 67.4% (58/86) | 82.7% (67/81)

5.3 Nephrotoxicity

In both the HABP/VABP trials and the cSSSI trials, renal adverse events were more likely to occur in patients with baseline comorbidities known to predispose patients to kidney dysfunction (pre-existing renal disease, diabetes mellitus, congestive heart failure, or hypertension). The renal adverse event rates were also higher in patients who received concomitant medications known to affect kidney function (e.g., non-steroidal anti-inflammatory drugs, ACE inhibitors, and loop diuretics).

Monitor renal function (i.e., serum creatinine, creatinine clearance) in all patients receiving VIBATIV. Values should be obtained prior to initiation of treatment, during treatment (at 48- to 72-hour intervals or more frequently, if clinically indicated), and at the end of therapy. If renal function decreases, the benefit of continuing VIBATIV versus discontinuing and initiating therapy with an alternative agent should be assessed [see Dosage and Administration (2), Adverse Reactions (6), and Clinical Pharmacology (12.3)].

In patients with renal dysfunction, accumulation of the solubilizer hydroxypropyl-beta-cyclodextrin can occur [see Patients with Renal Impairment (8.6) and Clinical Pharmacology (12.3)].

5.4 Embryo-Fetal Toxicity

Based on findings in animal reproduction studies, VIBATIV may cause fetal harm. VIBATIV caused adverse developmental outcomes in 3 animal species at clinically relevant doses. Verify pregnancy status in females of reproductive potential prior to initiating VIBATIV. Advise pregnant women of the potential risk to a fetus. Advise females of reproductive potential to use effective contraception during treatment with VIBATIV and for 2 days after the final dose [see Use in Specific Populations (8.1, 8.3)].

5.5 Coagulation Test Interference

Although telavancin does not interfere with coagulation, it interfered with certain tests used to monitor coagulation (Table 3), when conducted using samples drawn 0 to 18 hours after VIBATIV administration for patients being treated once every 24 hours. Blood samples for these coagulation tests should be collected as close as possible prior to a patient's next dose of VIBATIV. Blood samples for coagulation tests unaffected by VIBATIV may be collected at any time [see Drug Interactions (7.1)].

For patients who require aPTT monitoring while being treated with VIBATIV, a non-phospholipid dependent coagulation test such as a Factor Xa (chromogenic) assay or an alternative anticoagulant not requiring aPTT monitoring may be considered.

Table 3: Coagulation Tests Affected and Unaffected by Telavancin
Affected by Telavancin | Unaffected by Telavancin
Prothrombin time/international normalized ratio Activated partial thromboplastin time Activated clotting time Coagulation based factor X activity assay | Thrombin time Whole blood (Lee-White) clotting time Platelet aggregation study Chromogenic anti-factor Xa assay Functional (chromogenic) factor X activity assay Bleeding time D-dimer Fibrin degradation products

No evidence of increased bleeding risk has been observed in clinical trials with VIBATIV. Telavancin has no effect on platelet aggregation. Furthermore, no evidence of hypercoagulability has been seen, as healthy subjects receiving VIBATIV have normal levels of D-dimer and fibrin degradation products.

5.6 Hypersensitivity Reactions

Serious and sometimes fatal hypersensitivity reactions, including anaphylactic reactions, may occur after first or subsequent doses. Discontinue VIBATIV at first sign of skin rash, or any other sign of hypersensitivity. Telavancin is a semi-synthetic derivative of vancomycin; it is unknown if patients with hypersensitivity reactions to vancomycin will experience cross-reactivity to telavancin. VIBATIV should be used with caution in patients with known hypersensitivity to vancomycin [see Postmarketing Experience (6.2)].

5.7 Infusion-Related Reactions

VIBATIV is a lipoglycopeptide antibacterial agent and should be administered over a period of 60 minutes to reduce the risk of infusion-related reactions. Rapid intravenous infusions of the glycopeptide class of antimicrobial agents can cause “Red-man Syndrome”-like reactions including: flushing of the upper body, urticaria, pruritus, or rash.

Stopping or slowing the infusion may result in cessation of these reactions.

5.8 Clostridium difficile-Associated Diarrhea

Clostridium difficile-associated diarrhea (CDAD) has been reported with nearly all antibacterial agents and may range in severity from mild diarrhea to fatal colitis. Treatment with antibacterial agents alters the flora of the colon and may permit overgrowth of C. difficile.

C. difficile produces toxins A and B which contribute to the development of CDAD. Hyper-toxin-producing strains of C. difficile cause increased morbidity and mortality, since these infections can be refractory to antimicrobial therapy and may require colectomy. CDAD must be considered in all patients who present with diarrhea following antibiotic use. Careful medical history is necessary because CDAD has been reported to occur more than 2 months after the administration of antibacterial agents.

If CDAD is suspected or confirmed, ongoing antibiotic use not directed against C. difficile may need to be discontinued. Appropriate fluid and electrolyte management, protein supplementation, antibiotic treatment of C. difficile, and surgical evaluation should be instituted as clinically indicated.

5.9 Development of Drug-Resistant Bacteria

Prescribing VIBATIV in the absence of a proven or strongly suspected bacterial infection is unlikely to provide benefit to the patient and increases the risk of the development of drug-resistant bacteria.

As with other antibacterial drugs, use of VIBATIV may result in overgrowth of nonsusceptible organisms, including fungi. Patients should be carefully monitored during therapy. If superinfection occurs, appropriate measures should be taken.

5.10 QTc Prolongation

In a study involving healthy volunteers, doses of 7.5 and 15 mg/kg of VIBATIV prolonged the QTc interval [see Clinical Pharmacology (12.2)]. Caution is warranted when prescribing VIBATIV to patients taking drugs known to prolong the QT interval. Patients with congenital long QT syndrome, known prolongation of the QTc interval, uncompensated heart failure, or severe left ventricular hypertrophy were not included in clinical trials of VIBATIV. Use of VIBATIV should be avoided in patients with these conditions.

6 ADVERSE REACTIONS

The following serious adverse reactions are also discussed elsewhere in the labeling:

- Nephrotoxicity [see Warnings and Precautions (5.3)]
- Infusion-related reactions [see Warnings and Precautions (5.7)]
- Clostridium difficile-associated diarrhea [see Warnings and Precautions (5.8)]

Because clinical trials are conducted under widely varying conditions, adverse reaction rates observed in the clinical trials of a drug cannot be directly compared to rates in the clinical trials of another drug and may not reflect the rates observed in practice.

6.1 Clinical Trials Experience

Complicated Skin and Skin Structure Infections

The two Phase 3 cSSSI clinical trials (Trial 1 and Trial 2) for VIBATIV included 929 adult patients treated with VIBATIV at 10 mg/kg IV once daily. The mean age of patients treated with VIBATIV was 49 years (range 18-96). There was a slight male predominance (56%) in patients treated with VIBATIV, and patients were predominantly Caucasian (78%).

In the cSSSI clinical trials, <1% (8/929) patients who received VIBATIV died and <1% (8/938) patients treated with vancomycin died. Serious adverse events were reported in 7% (69/929) of patients treated with VIBATIV and most commonly included renal, respiratory, or cardiac events. Serious adverse events were reported in 5% (43/938) of vancomycin-treated patients, and most commonly included cardiac, respiratory, or infectious events. Treatment discontinuations due to adverse events occurred in 8% (72/929) of patients treated with VIBATIV, the most common events being nausea and rash (~1% each). Treatment discontinuations due to adverse events occurred in 6% (53/938) of vancomycin-treated patients, the most common events being rash and pruritus (~1% each).

The most common adverse events occurring in ≥10% of VIBATIV-treated patients observed in the VIBATIV Phase 3 cSSSI trials were taste disturbance, nausea, vomiting, and foamy urine.

Table 4 displays the incidence of treatment-emergent adverse drug reactions reported in ≥2% of patients treated with VIBATIV possibly related to the drug.

Table 4: Incidence of Treatment-Emergent Adverse Drug Reactions Reported in ≥2% of Patients Treated in cSSSI Trial 1 and Trial 2
 | VIBATIV (N=929) | Vancomycin (N=938)
Body as a Whole
Rigors | 4% | 2%
Digestive System
Nausea | 27% | 15%
Vomiting | 14% | 7%
Diarrhea | 7% | 8%
Metabolic and Nutritional
Decreased appetite | 3% | 2%
Nervous System
Taste disturbance* | 33% | 7%
Renal System
Foamy urine | 13% | 3%
*Described as metallic or soapy taste.

HABP/VABP

Two randomized, double-blind Phase 3 trials (Trial 1 and Trial 2) for VIBATIV included 1,503 adult patients treated with VIBATIV at 10 mg/kg IV once daily or vancomycin at 1 g IV twice daily. The mean age of patients treated with VIBATIV was 62 years (range 18-100) with 69% of the patients white and 65% male. In the combined VIBATIV group, 29% were VAP and 71% were HAP patients.

Table 5 summarizes deaths using Kaplan-Meier estimates at Day 28 as stratified by baseline creatinine clearance categorized into four groups. Patients with pre-existing moderate/severe renal impairment (CrCl ≤50 mL/min) who were treated with VIBATIV for HABP/VABP had increased mortality observed versus vancomycin in both the trials.

Table 5: 28-Day Mortality* Stratified by Baseline Creatinine Clearance- All-Treated Analysis Population
CrCl (mL/min) |  | Trial 1 |  |  | Trial 2
CrCl (mL/min) | VIBATIV N (%) | Vancomycin N (%) | Difference (95% CI) | VIBATIV N (%) | Vancomycin N (%) | Difference (95% CI)
>80 | 143 (12.2%) | 152 (14.1%) | -1.8 (-9.6, 6.0) | 181 (10.5%) | 181 (18.7%) | -8.2 (-15.5, -0.9)
>50-80 | 88 (27.4%) | 88 (17.7%) | 9.7 (-2.7, 22.1) | 96 (25.6%) | 90 (27.1%) | -1.5 (-14.4, 11.3)
30-50 | 80 (34.7%) | 83 (23.1%) | 11.5 (-2.5, 25.5) | 62 (27.7%) | 68 (23.7%) | 4.0 (-11.1, 19.1)
<30 | 61 (44.3%) | 51 (37.3%) | 7.0 (-11.2, 25.2) | 38 (61.1%) | 41 (42.1%) | 19.0 (-2.9, 40.8)
*(Kaplan-Meier Estimates)

Serious adverse events were reported in 31% of patients treated with VIBATIV and 26% of patients who received vancomycin. Treatment discontinuations due to adverse events occurred in 8% (60/751) of patients who received VIBATIV, the most common events being acute renal failure and electrocardiogram QTc interval prolonged (~1% each). Treatment discontinuations due to adverse events occurred in 5% (40/752) of vancomycin-patients, the most common events being septic shock and multi-organ failure (<1%).

Table 6 displays the incidence of treatment-emergent adverse drug reactions reported in ≥ 5% of HABP/VABP patients treated with VIBATIV possibly related to the drug.

Table 6: Incidence of Treatment Emergent Adverse Drug Reactions Reported in ≥5% of Patients Treated in HABP/VABP Trial 1 and Trial 2
 | VIBATIV (N=751) | Vancomycin (N=752)
Nausea | 5% | 4%
Vomiting | 5% | 4%
Renal Failure Acute | 5% | 4%

Nephrotoxicity

Complicated Skin and Skin Structure Infections

In cSSSI trials, the incidence of renal adverse events indicative of renal impairment (increased serum creatinine, renal impairment, renal insufficiency, and/or renal failure) was 30/929 (3%) of VIBATIV-treated patients compared with 10/938 (1%) of vancomycin-treated patients. In 17 of the 30 VIBATIV-treated patients, these adverse events had not completely resolved by the end of the trials, compared with 6 of the 10 vancomycin-treated patients. Serious adverse events indicative of renal impairment occurred in 11/929 (1%) of VIBATIV-treated patients compared with 3/938 (0.3%) of vancomycin-treated patients. Twelve patients treated with VIBATIV discontinued treatment due to adverse events indicative of renal impairment compared with 2 patients treated with vancomycin.

Increases in serum creatinine to 1.5 times baseline occurred more frequently among VIBATIV-treated patients with normal baseline serum creatinine (15%) compared with vancomycin-treated patients with normal baseline serum creatinine (7%).

Fifteen of 174 (9%) VIBATIV-treated patients ≥65 years of age had adverse events indicative of renal impairment compared with 16 of 755 patients (2%) <65 years of age [see Use in Specific Populations (8.5)].

Hospital-Acquired and Ventilator-Associated Bacterial Pneumonia

In the HABP/VABP trials, the incidence of renal adverse events (increased serum creatinine, renal impairment, renal insufficiency, and/or renal failure) was 10% for VIBATIV vs. 8% for vancomycin. Of the patients who had at least one renal adverse event, 54% in each treatment group recovered completely, recovered with sequelae, or were improving from the renal AE at the last visit. Three percent of VIBATIV-treated patients and 2% of vancomycintreated patients experienced at least one serious renal adverse event. Renal adverse events resulted in discontinuation of study medication in 14 VIBATIV-treated patients (2%) and 7 vancomycin-treated patients (1%).

Increases in serum creatinine to 1.5 times baseline occurred more frequently among VIBATIV-treated patients (16%) compared with vancomycin-treated patients (10%).

Forty-four of 399 (11.0%) VIBATIV-treated patients ≥65 years of age had adverse events indicative of renal impairment compared with 30 of 352 patients (8%) <65 years of age [see Use in Specific Populations (8.5)].

6.2 Postmarketing Experience

The following adverse reactions have been identified during post-approval use of VIBATIV. Because these events are reported voluntarily from a population of uncertain size, it is not always possible to reliably estimate their frequency or establish a causal relationship to drug exposure.

Serious hypersensitivity reactions have been reported after first or subsequent doses of VIBATIV, including anaphylactic reactions. It is unknown if patients with hypersensitivity reactions to vancomycin will experience crossreactivity to telavancin. [see Hypersensitivity Reactions (5.6)]

7 DRUG INTERACTIONS

7.1 Drug-Laboratory Test Interactions

Effects of Telavancin on Coagulation Test Parameters

Telavancin binds to the artificial phospholipid surfaces added to common anticoagulation tests, thereby interfering with the ability of the coagulation complexes to assemble on the surface of the phospholipids and promote clotting in vitro. These effects appear to depend on the type of reagents used in commercially available assays. Thus, when measured shortly after completion of an infusion of VIBATIV, increases in the PT, INR, aPTT, and ACT have been observed. These effects dissipate over time, as plasma concentrations of telavancin decrease.

Urine Protein Tests

Telavancin interferes with urine qualitative dipstick protein assays, as well as quantitative dye methods (e.g., pyrogallol red-molybdate). However, microalbumin assays are not affected and can be used to monitor urinary protein excretion during VIBATIV treatment.

8 USE IN SPECIFIC POPULATIONS

8.1 Pregnancy

Risk Summary

Based on findings in animal reproduction studies, VIBATIV may cause fetal harm. There are no available data on VIBATIV use in pregnant women to evaluate for a drug-associated risk of major birth defects, miscarriage, or adverse maternal or fetal outcomes. In embryo-fetal development studies in rats, rabbits, and minipigs, telavancin demonstrated the potential to cause limb and skeletal malformations when given intravenously during the period of organogenesis at doses providing approximately 1- to 2-fold the human exposure at the maximum recommended clinical dose (see Data). Advise pregnant women of the potential risk to a fetus. The estimated background risk of major birth defects and miscarriage for the indicated population is unknown.

All pregnancies have a background risk of birth defect, loss, or other adverse outcomes. In the U.S. general population, the estimated background risk of major birth defects and miscarriage in clinically recognized pregnancies is 2 to 4% and 15 to 20%, respectively.

Data

Animal Data

In embryo-fetal development studies in rats, rabbits, and minipigs, telavancin demonstrated the potential to cause limb and skeletal malformations when given intravenously during the period of organogenesis at doses up to 150, 45, or 75 mg/kg/day, respectively. These doses resulted in exposure levels approximately 1- to 2-fold the human exposure (AUC) at the maximum recommended clinical dose. Malformations observed at <1% (but absent or at lower rates in historical or concurrent controls), included brachymelia (rats and rabbits), syndactyly (rats, minipigs), adactyly (rabbits), and polydactyly (minipigs). Additional findings in rabbits included flexed front paw and absent ulna, and in the minipigs included misshapen digits and deformed front leg. Fetal body weights were decreased in rats.

In a prenatal/perinatal development study, pregnant rats received intravenous telavancin at up to 150 mg/kg/day (approximately the same AUC as observed at the maximum clinical dose) from the start of organogenesis through lactation. Offspring showed decreases in fetal body weight and an increase in the number of stillborn pups. Brachymelia was also observed. Developmental milestones and fertility of the pups were unaffected.

8.2 Lactation

Risk Summary

There are no data on the presence of telavancin in human milk, the effects on the breastfed child, or the effects on milk production. The developmental and health benefits of breastfeeding should be considered along with the mother's clinical need for VIBATIV and any potential adverse effects on the breastfed child from VIBATIV or from the underlying maternal conditions.

8.3 Females and Males of Reproductive Potential

Pregnancy Testing

Verify pregnancy status in females of reproductive potential prior to initiating VIBATIV.

Contraception

Females

VIBATIV may cause fetal harm when administered to a pregnant woman [see Use in Specific Populations (8.1)]. Advise females of reproductive potential to use effective contraception during treatment and for 2 days after the final dose.

Infertility

Males

Based on findings in rats, VIBATIV may impair male fertility [see Nonclinical Toxicology (13.1)]. The effect on fertility was reversible in rats.

8.4 Pediatric Use

The safety and effectiveness of VIBATIV have not been established in pediatric patients. In particular, there is a concern for poor clinical outcomes in pediatric patients less than one year of age due to immature renal function. Increased mortality in adult patients with HABP/VABP and renal impairment and decreased clinical response in adults with cSSSI and renal impairment were observed [see Boxed Warning and Warnings and Precautions (5.1, 5.2)].

8.5 Geriatric Use

Of the 929 patients treated with VIBATIV at a dose of 10 mg/kg once daily in clinical trials of cSSSI, 174 (19%) were ≥65 years of age and 87 (9%) were ≥75 years of age. In the cSSSI trials, lower clinical cure rates were observed in patients ≥65 years of age compared with those <65 years of age. Overall, treatment-emergent adverse events occurred with similar frequencies in patients ≥65 (75% of patients) and <65 years of age (83% of patients). Fifteen of 174 (9%) patients ≥65 years of age treated with VIBATIV had adverse events indicative of renal impairment compared with 16 of 755 (2%) patients <65 years of age [see Warnings and Precautions (5.3), Clinical Trials (14.1)].

Of the 749 HABP/VABP patients treated with VIBATIV at a dose of 10 mg/kg once daily in clinical trials of HABP/VABP, 397 (53%) were ≥65 years of age and 230 (31%) were ≥75 years of age. Treatment-emergent adverse events as well as deaths and other serious adverse events occurred more often in patients ≥65 years of age than in those <65 years of age in both treatment groups.

Telavancin is substantially excreted by the kidney, and the risk of adverse reactions may be greater in patients with impaired renal function. Because elderly patients are more likely to have decreased renal function, care should be taken in dose selection in this age group.

The mean plasma AUC values of telavancin were similar in healthy young and elderly subjects. Dosage adjustment for elderly patients should be based on renal function [see Dosage and Administration (2), Clinical Pharmacology (12.3)].

8.6 Patients with Renal Impairment

The HABP/VABP and cSSSI trials included patients with normal renal function and patients with varying degrees of renal impairment. Patients with underlying renal dysfunction or risk factors for renal dysfunction had a higher incidence of renal adverse events [see Warnings and Precautions (5.3)].

In the HABP/VABP studies higher mortality rates were observed in the VIBATIV-treated patients with baseline CrCl ≤50 mL/min. Use of VIBATIV in patients with pre-existing moderate/severe renal impairment should be considered only when the anticipated benefit to the patient outweighs the potential risk [see Warnings and Precautions (5.1,)].

VIBATIV-treated patients in the cSSSI studies with baseline creatinine clearance ≤50 mL/min had lower clinical cure rates. Consider these data when selecting antibacterial therapy in patients with baseline moderate/severe renal impairment (CrCl ≤50 mL/min) [see Warnings and Precautions (5.2)].

Dosage adjustment is required in patients with ≤50 mL/min renal impairment [see Dosage and Administration (2)]. There is insufficient information to make specific dosage adjustment recommendations for patients with end-stage renal disease (CrCl <10 mL/min), including patients receiving hemodialysis [see Overdosage (10), Clinical Pharmacology (12.3)].

Hydroxypropyl-beta-cyclodextrin is excreted in urine and may accumulate in patients with renal impairment. Serum creatinine should be closely monitored and, if renal toxicity is suspected, an alternative agent should be considered [see Warnings and Precautions (5.3), Clinical Pharmacology (12.3)].

8.7 Patients with Hepatic Impairment

The HABP/VABP and cSSSI trials included patients with normal hepatic function and with hepatic impairment. No dosage adjustment is recommended in patients with mild or moderate hepatic impairment [see Clinical Pharmacology (12.3)].

10 OVERDOSAGE

In the event of overdosage, VIBATIV should be discontinued and supportive care is advised with maintenance of glomerular filtration and careful monitoring of renal function. Following administration of a single dose of VIBATIV 7.5 mg/kg to subjects with end-stage renal disease, approximately 5.9% of the administered dose of telavancin was recovered in the dialysate following 4 hours of hemodialysis. However, no information is available on the use of hemodialysis to treat an overdosage [see Clinical Pharmacology (12.3)].

The clearance of telavancin by continuous venovenous hemofiltration (CVVH) was evaluated in an in vitro study [see Nonclinical Toxicology (13.2)]. Telavancin was cleared by CVVH and the clearance of telavancin increased with increasing ultrafiltration rate. However, the clearance of telavancin by CVVH has not been evaluated in a clinical study; thus, the clinical significance of this finding and use of CVVH to treat an overdosage is unknown.

11 DESCRIPTION

VIBATIV contains telavancin hydrochloride (Figure 1), a lipoglycopeptide antibacterial that is a synthetic derivative of vancomycin. The chemical name of telavancin hydrochloride is vancomycin, N3''-[2(decylamino-)ethyl]-29[[(phosphonomethyl)-amino]-methyl]-hydrochloride. Telavancin hydrochloride has the following chemical structure:

Figure 1: Telavancin Hydrochloride

Telavancin hydrochloride is an off-white to slightly colored amorphous powder with the empirical formula C80H106Cl2N11O27P•xHCl (where x = 1 to 3) and a free-base molecular weight of 1755.6. It is highly lipophilic and slightly soluble in water.

VIBATIV is a sterile, preservative-free, white to slightly colored lyophilized powder containing telavancin hydrochloride (equivalent to 750 mg of telavancin as the free base) for intravenous use. The inactive ingredients are Hydroxypropylbetadex, (hydroxypropyl-beta-cyclodextrin) (7500 mg per 750 mg telavancin), mannitol (937.5 mg per 750 mg telavancin), and sodium hydroxide and hydrochloric acid used in minimal quantities for pH adjustment. When reconstituted, it forms a clear to slightly colored solution with a pH of 4.5 (4.0 to 5.0).

12 CLINICAL PHARMACOLOGY

12.1 Mechanism of Action

Telavancin is an antibacterial drug [see Clinical Pharmacology (12.4)].

12.2 Pharmacodynamics

The antimicrobial activity of telavancin appears to best correlate with the ratio of area under the concentration-time curve to minimum inhibitory concentration (AUC/MIC) for Staphylococcus aureus based on animal models of infection. Exposure-response analyses of the clinical trials support the dose of 10 mg/kg every 24 hours.

Cardiac Electrophysiology

The effect of telavancin on cardiac repolarization was assessed in a randomized, double-blind, multiple-dose, positive-controlled, and placebo-controlled, parallel study (n=160). Healthy subjects received VIBATIV 7.5 mg/kg, VIBATIV 15 mg/kg, positive control, or placebo infused over 60 minutes once daily for 3 days. Based on interpolation of the data from VIBATIV 7.5 mg/kg and 15 mg/kg, the mean maximum baseline-corrected, placebocorrected QTc prolongation at the end of infusion was estimated to be 12-15 msec for VIBATIV 10 mg/kg and 22 msec for the positive control (Table 7). By 1 hour after infusion the maximum QTc prolongation was 6-9 msec for VIBATIV and 15 msec for the positive control.

Table 7: Mean and Maximum QTcF Changes from Baseline Relative to Placebo
 | QTcF^1 Change from Baseline
 | Mean (Upper 90% Confidence Limit^2) msec | Maximum (Upper 90% Confidence Limit) msec
VIBATIV 7.5 mg/kg | 4.1 (7) | 11.6 (16)
VIBATIV 15 mg/kg | 4.6 (8) | 15.1 (20)
Positive Control | 9.5 (13) | 21.6 (26)
^1 Fridericia corrected; ^2 Upper Confidence Limit (CL) from a 2-sided 90% Confidence Interval (CI) on difference from placebo (msec)

ECGs were performed prior to and during the treatment period in patients receiving VIBATIV 10 mg/kg in 3 cSSSI studies to monitor QTc intervals. In these trials, 214 of 1029 (21%) patients allocated to treatment with VIBATIV and 164 of 1033 (16%) allocated to vancomycin received concomitant medications known to prolong the QTc interval and known to be associated with definite or possible risk of torsades de pointes. The incidence of QTc prolongation >60 msec was 1.5% (15 patients) in the VIBATIV group and 0.6% (6 patients) in the vancomycin group. Nine of the 15 VIBATIV patients received concomitant medications known to prolong the QTc interval and definitely or possibly associated with a risk of torsades de pointes, compared with 1 of the 6 patients who received vancomycin. A similar number of patients in each treatment group (<1%) who did not receive a concomitant medication known to prolong the QTc interval experienced a prolongation >60 msec from baseline. In a separate analysis, 1 patient in the VIBATIV group and 2 patients in the vancomycin group experienced QTc >500 msec. No cardiac adverse events were ascribed to prolongation of the QTc interval. In the Phase 3 HABP/VABP studies, the incidence of QTc prolongation >60 msec or mean value >500 msec was 8% (52 patients) in the telavancin group and 7% (48 patients) in the vancomycin group.

12.3 Pharmacokinetics

The mean pharmacokinetic parameters of telavancin (10 mg/kg) after a single and multiple 60-minute intravenous infusions (10 mg/kg every 24 hours) are summarized in Table 8.

Table 8: Pharmacokinetic Parameters of Telavancin in Healthy Adults, 10 mg/kg
 | Single Dose (n=42) | Multiple Dose (n=36)
Cmax (mcg/mL) | 93.6 ± 14.2 | 108 ± 26
AUC0-∞ (mcg⋅hr/mL) | 747 ± 129 | --^1
AUC0-24h (mcg⋅hr/mL) | 666 ± 107 | 780 ± 125
t1/2 (hr) | 8.0 ± 1.5 | 8.1 ± 1.5
Cl (mL/hr/kg) | 13.9 ± 2.9 | 13.1 ± 2.0
Vss (mL/kg) | 145 ± 23 | 133 ± 24
Cmax = maximum plasma concentration; AUC = area under concentration-time course; t1/2 = terminal elimination half-life; Cl = clearance; Vss = apparent volume of distribution at steady state; --^1 Data not available

In healthy young adults, the pharmacokinetics of telavancin administered intravenously were linear following single doses from 5 to 12.5 mg/kg and multiple doses from 7.5 to 15 mg/kg administered once daily for up to 7 days. Steadystate concentrations were achieved by the third daily dose.

Distribution

Telavancin binds to human plasma proteins, primarily to serum albumin, in a concentration-independent manner. The mean binding is approximately 90% and is not affected by renal or hepatic impairment.

Concentrations of telavancin in pulmonary epithelial lining fluid (ELF) and alveolar macrophages (AM) were measured through collection of bronchoalveolar lavage fluid at various times following administration of VIBATIV 10 mg/kg once daily for 3 days to healthy adults. Telavancin concentrations in ELF and AM exceeded the MIC90 for S. aureus (0.5 mcg/mL) for at least 24 hours following dosing.

Concentrations of telavancin in skin blister fluid were 40% of those in plasma (AUC0-24hr ratio) after 3 daily doses of 7.5 mg/kg VIBATIV in healthy young adults.

Metabolism

No metabolites of telavancin were detected in in vitro studies using human liver microsomes, liver slices, hepatocytes, and kidney S9 fraction. None of the following recombinant CYP 450 isoforms were shown to metabolize telavancin in human liver microsomes: CYP 1A2, 2C9, 2C19, 2D6, 3A4, 3A5, 4A11. The clearance of telavancin is not expected to be altered by inhibitors of any of these enzymes.

In a mass balance study in male subjects using radiolabeled telavancin, 3 hydroxylated metabolites were identified with the predominant metabolite (THRX-651540) accounting for <10% of the radioactivity in urine and <2% of the radioactivity in plasma. The metabolic pathway for telavancin has not been identified.

Excretion

Telavancin is primarily eliminated by the kidney. In a mass balance study, approximately 76% of the administered dose was recovered from urine and <1% of the dose was recovered from feces (collected up to 216 hours) based on total radioactivity.

Specific Populations

Geriatric Patients

The impact of age on the pharmacokinetics of telavancin was evaluated in healthy young (range 21-42 years) and elderly (range 65-83 years) subjects. The mean CrCl of elderly subjects was 66 mL/min. Age alone did not have a clinically meaningful impact on the pharmacokinetics of telavancin [see Use in Specific Populations (8.5)].

Pediatric Patients

The pharmacokinetics of telavancin in patients less than 18 years of age have not been studied.

Gender

The impact of gender on the pharmacokinetics of telavancin was evaluated in healthy male (n=8) and female (n=8) subjects. The pharmacokinetics of telavancin were similar in males and females. No dosage adjustment is recommended based on gender.

Renal Impairment

The pharmacokinetics of telavancin were evaluated in subjects with normal renal function and subjects with varying degrees of renal impairment following administration of a single dose of telavancin 7.5 mg/kg (n=28). The mean AUC0-∞ values were approximately 13%, 29%, and 118% higher for subjects with CrCl >50 to 80 mL/min, CrCl 30 to 50 mL/min, and CrCl <30 mL/min, respectively, compared with subjects with normal renal function. Dosage adjustment is required in patients with CrCl ≤50 mL/min [see Dosage and Administration (2)].

Creatinine clearance was estimated from serum creatinine based on the Cockcroft-Gault formula:

CrCl = [140 – age (years)] x ideal body weight (kg)* {x 0.85 for female patients}
[72 x serum creatinine (mg/dL)]

*Use actual body weight if < ideal body weight (IBW)

IBW (male) = 50 kg + 0.9 kg/cm over 152 cm height

IBW (female) = 45.5 kg + 0.9 kg/cm over 152 cm height

Following administration of a single dose of VIBATIV 7.5 mg/kg to subjects with end-stage renal disease, approximately 5.9% of the administered dose of telavancin was recovered in the dialysate following 4 hours of hemodialysis. The effects of peritoneal dialysis have not been studied.

Following a single intravenous dose of VIBATIV 7.5 mg/kg, the clearance of hydroxypropyl-beta-cyclodextrin was reduced in subjects with renal impairment, resulting in a higher exposure to hydroxypropyl-beta-cyclodextrin. In subjects with mild, moderate, and severe renal impairment, the mean clearance values were 38%, 59%, and 82% lower, respectively, compared with subjects with normal renal function. Multiple infusions of VIBATIV may result in accumulation of hydroxypropyl-beta-cyclodextrin.

Hepatic Impairment

The pharmacokinetics of telavancin were not altered in subjects with moderate hepatic impairment (n= 8, Child-Pugh B) compared with healthy subjects with normal hepatic function matched for gender, age, and weight. The pharmacokinetics of telavancin have not been evaluated in patients with severe hepatic impairment (Child-Pugh C).

Drug Interactions

In Vitro

The inhibitory activity of telavancin against the following CYP 450 enzymes was evaluated in human liver microsomes: CYP 1A2, 2C9, 2C19, 2D6, and 3A4/5. Telavancin inhibited CYP 3A4/5 at potentially clinically relevant concentrations. Upon further evaluation in a Phase 1 clinical trial, telavancin was found not to inhibit the metabolism of midazolam, a sensitive CYP3A substrate (see below).

Midazolam

The impact of telavancin on the pharmacokinetics of midazolam (CYP 3A4/5 substrate) was evaluated in 16 healthy adult subjects following administration of a single dose of VIBATIV 10 mg/kg, intravenous midazolam 1 mg, and both. The results showed that telavancin had no impact on the pharmacokinetics of midazolam and midazolam had no effect on the pharmacokinetics of telavancin.

Aztreonam

The impact of telavancin on the pharmacokinetics of aztreonam was evaluated in 11 healthy adult subjects following administration of a single dose of VIBATIV 10 mg/kg, aztreonam 2 g, and both. Telavancin had no impact on the pharmacokinetics of aztreonam and aztreonam had no effect on the pharmacokinetics of telavancin. No dosage adjustment of telavancin or aztreonam is recommended when both drugs are coadministered.

Piperacillin-tazobactam

The impact of telavancin on the pharmacokinetics of piperacillin-tazobactam was evaluated in 12 healthy adult subjects following administration of a single dose of VIBATIV 10 mg/kg, piperacillin-tazobactam 4.5 g, and both. Telavancin had no impact on the pharmacokinetics of piperacillin-tazobactam and piperacillin-tazobactam had no effect on the pharmacokinetics of telavancin. No dosage adjustment of telavancin or piperacillin-tazobactam is recommended when both drugs are coadministered.

12.4 Microbiology

Telavancin is a semisynthetic, lipoglycopeptide antibiotic. Telavancin exerts concentration-dependent, bactericidal activity against Gram-positive organisms in vitro, as demonstrated by time-kill assays and MBC/MIC (minimum bactericidal concentration/minimum inhibitory concentration) ratios using broth dilution methodology. In vitro studies demonstrated a telavancin post-antibiotic effect ranging from 1 to 6 hours against S. aureus and other Grampositive pathogens.

Mechanism of Action

Telavancin inhibits cell wall biosynthesis by binding to late-stage peptidoglycan precursors, including lipid II. Telavancin also binds to the bacterial membrane and disrupts membrane barrier function.

Interactions with Other Antibacterial Drugs

In vitro investigations demonstrated no antagonism between telavancin and amikacin, aztreonam, cefepime, ceftriaxone, ciprofloxacin, gentamicin, imipenem, meropenem, oxacillin, piperacillin/tazobactam, rifampin, and trimethoprim/sulfamethoxazole when tested in various combinations against telavancin-susceptible staphylococci, streptococci, and enterococci. This information is not available for other bacteria.

Cross-Resistance

Some vancomycin-resistant enterococci have a reduced susceptibility to telavancin. There is no known crossresistance between telavancin and other classes of antibacterial drugs.

Antibacterial Activity

Telavancin has been shown to be active against most isolates of the following microorganisms both in vitro and in clinical infections as described in the Indications and Usage section [see Indications and Usage (1)]:

Gram-Positive Bacteria

Staphylococcus aureus (including methicillin-resistant isolates)

Enterococcus faecalis (vancomycin-susceptible isolates only)

Streptococcus agalactiae

Streptococcus anginosus group (includes S. anginosus, S. intermedius, and S. constellatus)

Streptococcus pyogenes

Greater than 90% of the following microorganisms exhibit an in vitro MIC less than or equal to the telavancinsusceptible breakpoint for organisms of similar genus. The safety and effectiveness of telavancin in treating clinical infections due to these microorganisms have not been established in adequate and well-controlled clinical trials.

Gram-Positive Bacteria

Enterococcus faecium (vancomycin-susceptible isolates only)

Staphylococcus haemolyticus

Streptococcus dysgalactiae subsp. equisimilis

Staphylococcus epidermidis

Susceptibility Testing

For specific information regarding susceptibility test interpretive criteria and associated test methods and quality control standards recognized by FDA for this drug, please see: https://www.fda.gov/STIC.

13 NONCLINICAL TOXICOLOGY

13.1 Carcinogenesis, Mutagenesis, Impairment of Fertility

Long-term studies in animals to determine the carcinogenic potential of telavancin have not been performed.

Neither mutagenic nor clastogenic potential of telavancin was found in a battery of tests including: assays for mutagenicity (Ames bacterial reversion), an in vitro chromosome aberration assay in human lymphocytes, and an in vivo mouse micronucleus assay.

Telavancin did not affect the fertility or reproductive performance of adult male rats (up to 100 mg/kg/day for at least 4 weeks prior to mating) or female rats (up to 150 mg/kg/day for at least 2 weeks prior to mating).

Male rats given 50 or 100 mg/kg/day telavancin for 6 weeks, at exposure levels similar to those measured in clinical studies, displayed altered sperm parameters that were reversible following an 8-week recovery period. A longer dosing period showed that telavancin caused histopathological changes in the seminiferous tubules and epididymides of the rat testis after 13 weeks of administration at 50 or 100 mg/kg/day. These changes were reversible at the end of a 4 week recovery period.

13.2 Animal Toxicology and/or Pharmacology

Two-week administration of telavancin in rats produced minimal renal tubular vacuolization with no changes in BUN or creatinine. These effects were not seen in studies conducted in dogs for similar duration. Four weeks of treatment resulted in reversible elevations in BUN and/or creatinine in association with renal tubular degeneration that further progressed following 13 weeks of treatment.

These effects occurred at exposures (based on AUCs) that were similar to those measured in clinical trials.

The potential effects of continuous venovenous hemofiltration (CVVH) on the clearance of telavancin were examined in an in vitro model using bovine blood. Telavancin was cleared by CVVH and the clearance of telavancin increased with increasing ultrafiltration rate [see Overdosage (10)].

14 CLINICAL STUDIES

14.1 Complicated Skin and Skin Structure Infections

Adult patients with clinically documented complicated skin and skin structure infections (cSSSI) were enrolled in two randomized, multinational, multicenter, double-blinded trials (Trial 1 and Trial 2) comparing VIBATIV (10 mg/kg IV every 24 hours) with vancomycin (1 g IV every 12 hours) for 7 to 14 days. Vancomycin dosages could be adjusted per site-specific practice. Patients could receive concomitant aztreonam or metronidazole for suspected Gram-negative and anaerobic infection, respectively. These trials were identical in design, enrolling approximately 69% of their patients from the United States.

The trials enrolled adult patients with cSSSI with suspected or confirmed MRSA as the primary cause of infection. The all-treated efficacy (ATe) population included all patients who received any amount of study medication according to their randomized treatment group and were evaluated for efficacy. The clinically evaluable population (CE) included patients in the ATe population with sufficient adherence to the protocol.

The ATe population consisted of 1,794 patients. Of these, 1,410 (79%) patients were clinically evaluable (CE). Patient baseline infection types were well-balanced between treatment groups and are presented in Table 9.

Table 9: Baseline Infection Types in cSSSI Trials 1 and 2 – ATe Population
 | VIBATIV (N=884)^1 | Vancomycin (N=910)^1
Type of infection
Major Abscess | 375 (42.4%) | 397 (43.6%)
Deep/Extensive Cellulitis | 309 (35.0%) | 337 (37.0%)
Wound Infection | 139 (15.7%) | 121 (13.3%)
Infected Ulcer | 45 (5.1%) | 46 (5.1%)
Infected Burn | 16 (1.8%) | 9 (1.0%)
^1 Includes all patients randomized, treated, and evaluated for efficacy

The primary efficacy endpoints in both trials were the clinical cure rates at a follow-up (Test-of-Cure) visit in the ATe and CE populations. Clinical cure rates in Trials 1 and 2 are displayed for the ATe and CE population in Table 10.

Table 10: Clinical Cure at Test-of-Cure in cSSSI Trials 1 and 2 – ATe and CE Populations
 | Trial 1 |  |  | Trial 2
 | VIBATIV | Vancomycin | Difference | VIBATIV | Vancomycin | Difference
 | % (n/N) | % (n/N) | (95% CI)^1 | % (n/N) | % (n/N) | (95% CI)^1
ATe | 72.5% (309/426) | 71.6% (307/429) | 0.9 (-5.3, 7.2) | 74.7% (342/458) | 74.0% (356/481) | 0.7 (-5.1, 6.5)
CE | 84.3% (289/343) | 82.8% (288/348) | 1.5 (-4.3, 7.3) | 83.9% (302/360) | 87.7% (315/359) | -3.8 (-9.2, 1.5)
^195% CI computed using a continuity correction

The cure rates by pathogen for the microbiologically evaluable (ME) population are presented in Table 11.

Table 11: Clinical Cure Rates at the Test-of-Cure for the Most Common Pathogens in cSSSI Trials 1 and 2 – ME Population^1
 | VIBATIV % (n/N) | Vancomycin % (n/N)
Staphylococcus aureus (MRSA) | 87.0% (208/239) | 85.9% (225/262)
Staphylococcus aureus (MSSA) | 82.0% (132/161) | 85.1% (131/154)
Enterococcus faecalis | 95.6% (22/23) | 80.0% (28/35)
Streptococcus pyogenes | 84.2% (16/19) | 90.5% (19/21)
Streptococcus agalactiae | 73.7% (14/19) | 86.7% (13/15)
Streptococcus anginosus group | 76.5% (13/17) | 100.0% (9/9)
^1 The ME population included patients in the CE population who had Gram-positive pathogens isolated at baseline and had central identification and susceptibility of the microbiological isolate(s).

Of the 1784 patients in the ATe population in the two cSSSI trials, 32 patients had baseline S. aureus bacteremia: 21 patients (2.4%, including 13 with MRSA) were treated with VIBATIV and 11 patients (1.2%, including 4 with MRSA) were treated with vancomycin. In these bacteremic patients, the clinical cure rate at Test-of-Cure was 57.1% (12/21) for the VIBATIV-treated patients and 54.6% (6/11) for the vancomycin-treated patients. Given the limited sample size in this subgroup, the interpretation of these results is limited.

In the two cSSSI trials, clinical cure rates were similar across gender and race. Clinical cure rates in the VIBATIV clinically evaluable (CE) population were lower in patients ≥65 years of age compared with those <65 years of age. A decrease of this magnitude was not observed in the vancomycin CE population. Clinical cure rates in the VIBATIV CE population <65 years of age were 503/581 (87%) and in those ≥65 years were 88/122 (72%). In the vancomycin CE population clinical cure rates in patients <65 years of age were 492/570 (86%) and in those ≥65 years was 111/137 (82%). Clinical cure rates in the VIBATIV-treated patients were lower in patients with baseline CrCl ≤50 mL/min compared with those with CrCl >50 mL/min. A decrease of this magnitude was not observed in the vancomycintreated patients [see Warnings and Precautions (5.2)].

14.2 HABP/VABP

Adult patients with hospital-acquired and ventilator-associated pneumonia were enrolled in two randomized, parallelgroup, multinational, multicenter, double-blinded trials of identical design comparing VIBATIV (10 mg/kg IV every 24 hours) with vancomycin (1 g IV every 12 hours) for 7 to 21 days. Vancomycin dosages could be adjusted for body weight and/or renal function per local guidelines. Patients could receive concomitant aztreonam or metronidazole for suspected Gram-negative and anaerobic infection, respectively. The addition of piperacillin/tazobactam was also permitted for coverage of Gram-negative organisms if resistance to aztreonam was known or suspected. Patients with known or suspected infections due to methicillin-resistant Staphylococcus aureus were enrolled in the studies.

Of the patients enrolled across both trials, 64% were male and 70% were white. The mean age was 63 years. At baseline, more than 50% were admitted to an intensive care unit, about 23% had chronic obstructive pulmonary disease, about 29% had ventilator-associated pneumonia and about 6% had bacteremia. Demographic and baseline characteristics were generally well-balanced between treatment groups; however, there were differences between HABP/VABP Trial 1 and HABP/VABP Trial 2 with respect to a baseline history of diabetes mellitus (31% in Trial 1, 21% in Trial 2) and baseline renal insufficiency (CrCl ≤ 50 mL/min) (36% in Trial 1, 27% in Trial 2).

All-cause mortality was evaluated because there is historical evidence of treatment effect for this endpoint. This was a protocol pre-specified secondary endpoint. The 28-day all-cause mortality outcomes (overall and by baseline creatinine clearance categorization) in the group of patients who had at least one baseline Gram-positive respiratory pathogen are shown in Table 12. This group of patients included those who had mixed Gram-positive/Gram-negative infections.

Table 12: All-Cause Mortality at Day 28 in Patients with at Least One Baseline Gram- Positive Pathogen
 |  | Trial 1 |  | Trial 2
 |  | VIBATIV | Vancomycin | VIBATIV | Vancomycin
All Patients | Mortalitya | 28.7% N=187 | 24.3% N=180 | 24.3% N=224 | 22.3% N=206
All Patients | Difference (95% CI) | 4.4% (-4.7%, 13.5%) |  | 2.0% (-6.1%, 10%)
CrCl ≤ 50 mL/min | Mortalitya | 41.8% N=63 | 35.4% N=68 | 43.9% N=53 | 29.6% N=58
CrCl ≤ 50 mL/min | Difference (95% CI) | 6.4% (-10.4, 23.2) |  | 14.3% (-3.6, 32.2)
CrCl > 50 mL/min | Mortalitya | 22.0% N=124 | 17.6% N=112 | 18.2% N=171 | 19.3% N=148
CrCl > 50 mL/min | Difference (95% CI) | 4.4% (-5.9, 14.7) |  | -1.1% (-9.8, 7.6)
aMortality rates are based on Kaplan-Meier estimates at Study Day 28. There were 84 patients (5.6%) whose survival statuses were not known up to 28 days after initiation of study drug and were considered censored at the last day known to be alive. Thirty-five of these patients were treated with VIBATIV and 45 were treated with vancomycin.

The protocol-specified analysis included clinical cure rates at the TOC (7 to 14 days after the last dose of study drug) in the co-primary All-Treated (AT) and Clinically Evaluable (CE) populations (Table 13). Clinical cure was determined by resolution of signs and symptoms, no further antibacterial therapy for HABP/VABP after end-oftreatment, and improvement or no progression of baseline radiographic findings. However, the quantitative estimate of treatment effect for this endpoint has not been established.

Table 13: Clinical Response Rates in Trials 1 and 2 – AT and CE Populations
 | Trial 1 |  | Trial 2
 | VIBATIV | Vancomycin | VIBATIV | Vancomycin
ATa Difference (95% CI) | 57.5% (214/372) | 59.1% (221/374) | 60.2% (227/377) | 60.0% (228/380)
ATa Difference (95% CI) | -1.6% (-8.6%, 5.5%) |  | 0.2% (-6.8%, 7.2%)
CEb Difference (95% CI) | 83.7% (118/141) | 80.2% (138/172) | 81.3% (139/171) | 81.2% (138/170)
CEb Difference (95% CI) | 3.5% (-5.1%, 12.0%) |  | 0.1% (-8.2%, 8.4%)
aAll-Treated (AT) Population: Patients who received at least one dose of study medication
bClinically Evaluable (CE) Population: Patients who were clinically evaluable

Among the 797 patients with at least one Gram-positive respiratory pathogen at baseline, 73 patients had concurrent S. aureus bacteremia: 35 patients (8.5%, including 21 with MRSA) were treated with VIBATIV and 38 patients (9.8%, including 24 with MRSA) were treated with vancomycin. In these bacteremic patients, the 28-day all-cause mortality rate was 40.0% (14/35) for VIBATIV-treated patients and 39.5% (15/38) for vancomycin-treated patients. Given the limited sample size in this subgroup, the interpretation of these results is limited.

16 HOW SUPPLIED/STORAGE AND HANDLING

- Individual cartons of 750 mg single-dose vials (NDC 66220-315-11)
- Cartons of 12 individually packaged 750 mg single-dose vials (NDC 66220-315-22); cartons of 4 individually packaged 750 mg single-dose vials (NDC 66220-315-44)

Store original packages at refrigerated temperatures of 2°C to 8°C (35°F to 46°F). Excursions to ambient temperatures (up to 25°C (77°F) are acceptable. Avoid excessive heat.

17 PATIENT COUNSELING INFORMATION

Advise the patient to read the FDA-approved patient labeling (Medication Guide).

Embryo-Fetal Toxicity

Advise pregnant women and females of reproductive potential of the potential risk to a fetus. Advise females to inform their healthcare provider of a known or suspected pregnancy [see Warnings and Precautions (5.4) and Use in Specific Populations (8.1, 8.3)].

Advise female patients of reproductive potential to use effective contraception during treatment with VIBATIV and for 2 days after the final dose [see Use in Specific Populations (8.3)]

Diarrhea

Diarrhea is a common problem caused by antibiotics that usually ends when the antibiotic is discontinued. Sometimes after starting treatment with antibiotics, patients can develop watery and bloody stools (with or without stomach cramps and fever) even as late as 2 or more months after having received the last dose of the antibiotic. If this occurs, patients should contact their physician as soon as possible.

Antibacterial Resistance

Patients should be counseled that antibacterial drugs including VIBATIV should only be used to treat bacterial infections. They do not treat viral infections (e.g., the common cold). When VIBATIV is prescribed to treat a bacterial infection, patients should be told that although it is common to feel better early in the course of therapy, the medication should be taken exactly as directed. Skipping doses or not completing the full course of therapy may: (1) decrease the effectiveness of immediate treatment, and (2) increase the likelihood that the bacteria will develop resistance and will not be treatable by VIBATIV or other antibacterial drugs in the future.

Common Adverse Effects

Patients should be informed about the common adverse effects of VIBATIV including diarrhea, taste disturbance, nausea, vomiting, headache, and foamy urine. Patients should be instructed to inform their healthcare provider if they develop any unusual symptom, or if any known symptom persists or worsens. Patients should be instructed to inform their healthcare provider of any other medications they are currently taking with VIBATIV, including over-thecounter medications.

Manufactured for:

Cumberland Pharmaceuticals Inc.

Nashville, TN 37203

US Patent Nos. 6,635,618 B2; 6,858,584 B2; 6,872,701 B2; 7,008,923 B2; 7,208,471 B2; 7,351,691 B2; 7,531,623 B2; 7,544,364 B2; 7,700,550 B2; 8,101,575 B2; 8,158,580 B2.

VIBATIV® and the VIBATIV® logo are a registered trademark of Cumberland Pharmaceuticals Inc.

MEDICATION GUIDE
VIBATIV® (vy-'ba-tiv)
(telavancin)
for injection, for intravenous use

Read this Medication Guide before you receive VIBATIV. This information does not take the place of talking to your healthcare provider about your medical condition or your treatment.

What is the most important information I should know about VIBATIV?
VIBATIV can cause serious side effects, including:

- Increased risk of death. VIBATIV was associated with an increased risk of death compared to vancomycin in people who already had kidney problems and were treated for bacterial pneumonia that you can get when you are in the hospital.
- New or worsening kidney problems. Your healthcare provider should do a blood test to check your kidneys before you start, while you receive, and after you stop receiving VIBATIV.
- VIBATIV may harm your unborn baby. If you are a woman who can become pregnant, your healthcare provider should do a pregnancy test before you start receiving VIBATIV.
  - Talk to your healthcare provider if you are pregnant or plan to become pregnant. Your healthcare provider will decide if VIBATIV is the right medicine for you.
  - Women who can become pregnant should use effective birth control (contraception) while receiving VIBATIV and for 2 days after the last dose of VIBATIV. Talk to your healthcare provider if you have questions about birth control.

What is VIBATIV?
VIBATIV is a prescription antibacterial medicine used alone, or with other medicines, to treat adults with certain types of germs (bacteria) that cause:

- serious skin infections
- Hospital-Acquired Bacterial Pneumonia (HABP)
- Ventilator-Associated Bacterial Pneumonia (VABP)

It is not known if VIBATIV is safe or effective in children.

Who should not receive VIBATIV? Do not receive VIBATIV if you:

- are allergic to telavancin or any of the ingredients in VIBATIV. See the end of this Medication Guide for a complete list of ingredients in VIBATIV.

What should I tell my healthcare provider before receiving VIBATIV?
Before you receive VIBATIV, tell your healthcare provider about all of your medical conditions, including if you:

- have had a serious allergic reaction to VIBATIV or vancomycin.
- have kidney problems.
- have diabetes.
- have, have had or have a family history of heart problems, including QTc prolongation.
- have high blood pressure.
- are pregnant or plan to become pregnant. See “What is the most important information I should know about VIBATIV?”
- are breastfeeding or plan to breastfeed. It is not known if VIBATIV passes into breast milk. You and your healthcare provider should decide if you will breastfeed while receiving VIBATIV.

Tell your healthcare provider about all the medicines you take, including prescription and over-the-counter medicines, vitamins, and herbal supplements. VIBATIV and other medicines can affect each other causing side effects. Especially tell your healthcare provider if you take:

- a Non-Steroidal Anti-Inflammatory Drug (NSAID)
- certain blood pressure medicines called Angiotensin-Converting Enzyme (ACE) Inhibitors or Angiotensin Receptor Blockers (ARBs)
- water pills (diuretics)
- a blood thinner
- medicine to control your heart rate or rhythm (antiarrhythmics)

Ask your healthcare provider or pharmacist for a list of these medicines, if you are not sure.
Know the medicines you take. Keep a list of your medicines and show it to your healthcare provider and pharmacist when you get a new medicine.

How will I receive VIBATIV?

- VIBATIV is given by your healthcare provider through a needle placed into your vein (IV infusion) slowly over 1 hour, 1 time each day, for 7 to 21 days.
- Do not stop receiving VIBATIV unless your healthcare provider tells you to, even if you feel better.
- Your healthcare provider will do blood tests before you start and while you receive VIBATIV.

What are the possible side effects of VIBATIV?
VIBATIV may cause serious side effects, including:
See “What is the most important information I should know about VIBATIV?”

- Serious allergic reactions. Allergic reactions can happen in people who receive VIBATIV, even after only 1 dose. Stop receiving VIBATIV and get emergency medical help right away if you get any of the following symptoms of a severe allergic reaction:

- hives
- trouble breathing or swallowing
- swelling of the lips, tongue, face

- throat tightness, hoarseness
- rapid heartbeat
- faint

- Infusion-related reactions. People who receive VIBATIV too quickly can have a certain type of skin reaction called “Redman Syndrome”. Signs and symptoms of Red-man Syndrome can include:

- red color (flushing)
- rash

- itching

- Problems with the electrical system of your heart (QTc prolongation). Tell your healthcare provider right away if you have a change in your heartbeat such as a fast or irregular heartbeat or if you had a fainting episode.

Call your healthcare provider right away if you have any of the serious side effects listed above.
The most common side effects of VIBATIV include:

- change in your sense of taste
- nausea
- vomiting

- foamy urine
- diarrhea

Tell your healthcare provider about any side effect that bothers you or that does not go away. These are not all the possible side effects of VIBATIV. For more information, ask your healthcare provider or pharmacist.
Call your doctor for medical advice about side effects. You may report side effects to FDA at 1-800-FDA-1088.

General information about the safe and effective use of VIBATIV.
Medicines are sometimes prescribed for purposes other than those listed in a Medication Guide.
This Medication Guide summarizes the most important information about VIBATIV. If you would like more information, talk with your healthcare provider. You can ask your pharmacist or healthcare provider for information about VIBATIV that is written for health professionals.

What are the ingredients in VIBATIV?
Active ingredient: telavancin hydrochloride
Inactive ingredients: hydroxypropylbetadex, Ph. Eur (hydroxypropyl-beta-cyclodextrin), mannitol, sodium hydroxide and hydrochloric acid
Manufactured for: Cumberland Pharmaceuticals Inc.
Marketed by: Cumberland Pharmaceuticals Inc., Nashville, TN 37203
VIBATIV® is a registered trademark of Cumberland Pharmaceuticals Inc.
For more information about VIBATIV, go to www.vibativ.com or call 1-877-683-6110.

This Medication Guide has been approved by the U.S. Food and Drug Administration

Revised: 01/2021

Principal Display Panel - 750 mg/vial Carton Label

NDC 66220-315-11

VIBATIV®
(telavancin) for injection

750 mg/
vial

Rx Only

Single Dose Vial-
Discard Unused Portion

Prior to Reconstitution: Store at 2
to 8°C (36° to 46°F).

After Reconstitution: Use within 12
hours at room temperature or within
7 days at 2 to 8°C (36° to 46°F)

See Package Insert for complete
directions for use.

CUMBERLAND®
PHARMACEUTICALS

Principal Display Panel - 750 mg/vial Vial Label

NDC 66220-315-11

VIBATIV®

(telavancin) for injection

750 mg/vial

For Intravenous Infusion Only

Single Dose Vial-

Discard Unused Portion

ATTENTION: Dispense with enclosed
Medication Guide.

Rx Only

CUMBERLAND®
PHARMACEUTICALS